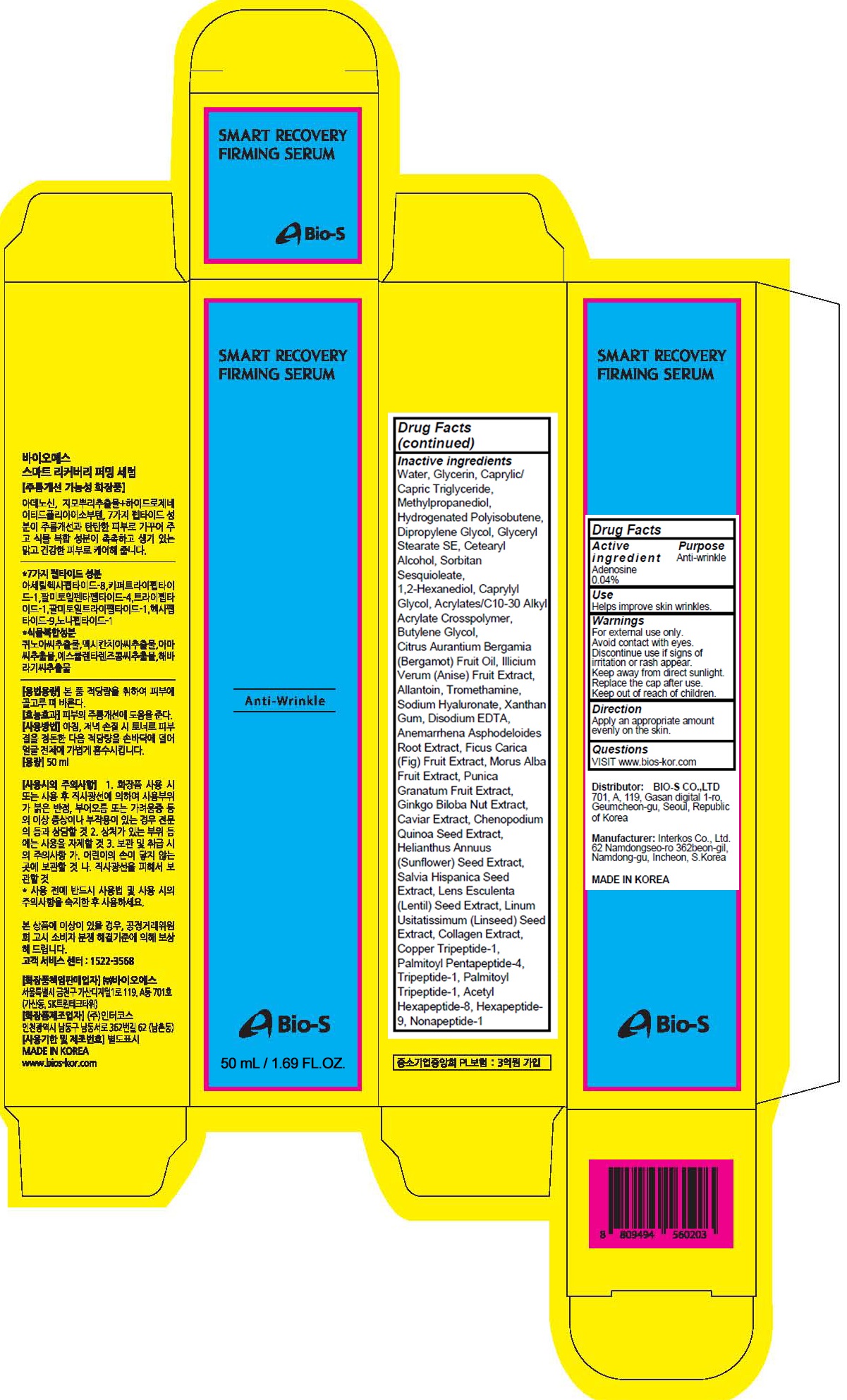 DRUG LABEL: SMART RECOVERY FIRMING SERUM
NDC: 81211-040 | Form: LIQUID
Manufacturer: BIO-S CO.,LTD
Category: otc | Type: HUMAN OTC DRUG LABEL
Date: 20201215

ACTIVE INGREDIENTS: Adenosine 0.02 g/50 mL
INACTIVE INGREDIENTS: Water; Glycerin; MEDIUM-CHAIN TRIGLYCERIDES; Methylpropanediol; HYDROGENATED POLYBUTENE (1300 MW); Dipropylene Glycol

ACTIVE INGREDIENT

Adenosine 0.04%

PURPOSE

Anti-wrinkle

Use

Helps improve skin wrinkles.

WARNINGS

For external use only.
Avoid contact with eyes.
Discontinue use if signs of irritation or rash appear.
Keep away from direct sunlight.
Replace the cap after use.
Keep out of reach of children.

KEEP OUT OF REACH OF CHILDREN

Direction

Apply an appropriate amount evenly on the skin.

QUESTIONS

VISIT www.bios-kor.com

INACTIVE INGREDIENTS

Water, Glycerin, Caprylic/Capric Triglyceride, Methylpropanediol, Hydrogenated Polyisobutene, Dipropylene Glycol, Glyceryl Stearate SE, Cetearyl Alcohol, Sorbitan Sesquioleate, 1,2-Hexanediol, Caprylyl Glycol, Acrylates/C10-30 Alkyl Acrylate Crosspolymer, Butylene Glycol, Citrus Aurantium Bergamia (Bergamot) Fruit Oil, Illicium Verum (Anise) Fruit Extract, Allantoin, Tromethamine, Sodium Hyaluronate, Xanthan Gum, Disodium EDTA, Anemarrhena Asphodeloides Root Extract, Ficus Carica (Fig) Fruit Extract, Morus Alba Fruit Extract, Punica Granatum Fruit Extract, Ginkgo Biloba Nut Extract, Caviar Extract, Chenopodium Quinoa Seed Extract, Helianthus Annuus (Sunflower) Seed Extract, Salvia Hispanica Seed Extract, Lens Esculenta (Lentil) Seed Extract, Linum Usitatissimum (Linseed) Seed Extract, Collagen Extract, Copper Tripeptide-1, Palmitoyl Pentapeptide-4, Tripeptide-1, Palmitoyl Tripeptide-1, Acetyl Hexapeptide-8, Hexapeptide-9, Nonapeptide-1